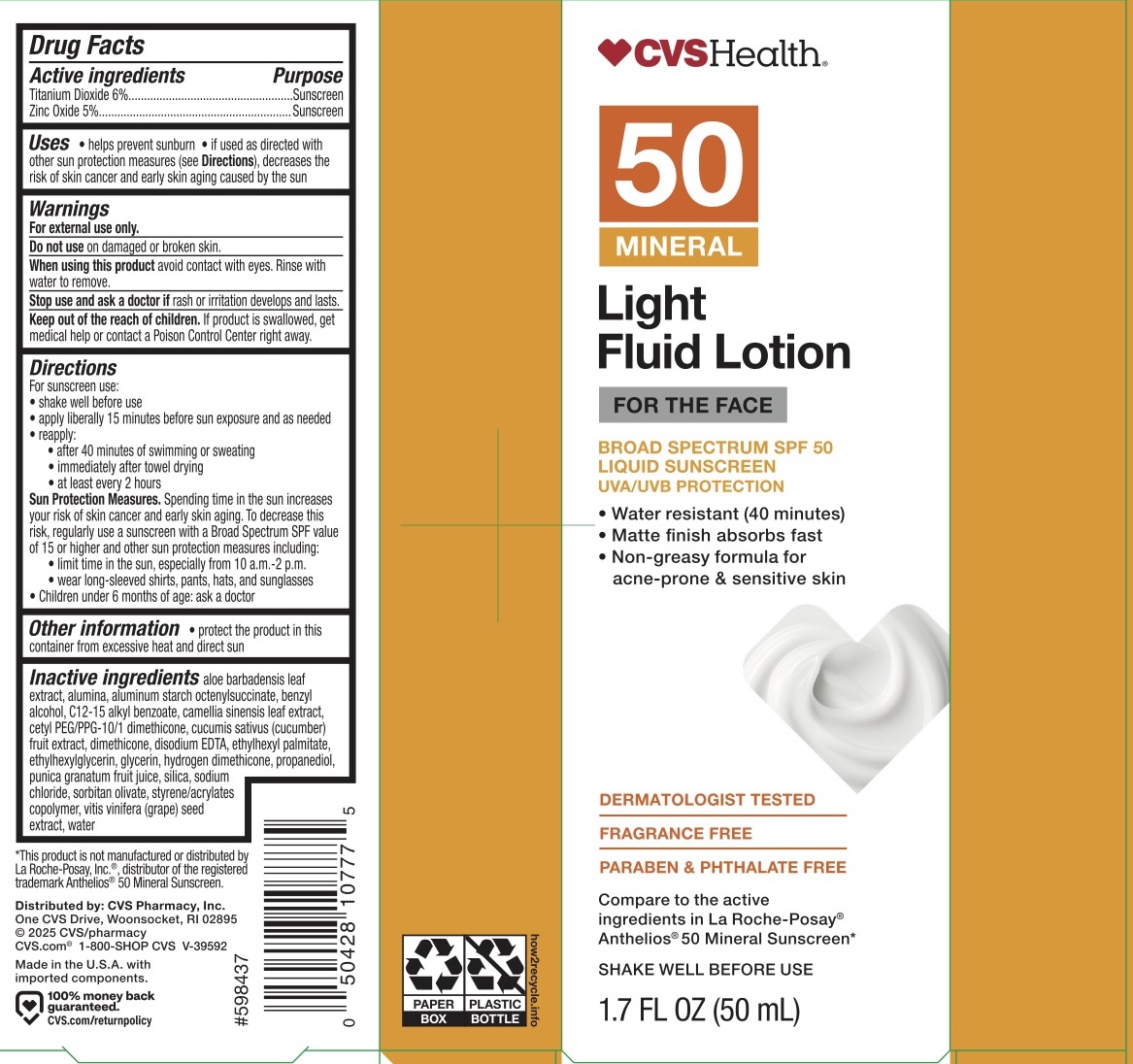 DRUG LABEL: CVS SPF 50 Face Sunscreen
NDC: 51316-217 | Form: LOTION
Manufacturer: CVS
Category: otc | Type: HUMAN OTC DRUG LABEL
Date: 20250916

ACTIVE INGREDIENTS: ZINC OXIDE 5 g/100 mL; TITANIUM DIOXIDE 6 g/100 mL
INACTIVE INGREDIENTS: ALUMINUM STARCH OCTENYLSUCCINATE; GLYCERIN; HYDROGEN DIMETHICONE (40 CST); PROPANEDIOL; SODIUM CHLORIDE; WATER; EDETATE DISODIUM; ETHYLHEXYL PALMITATE; BENZYL ALCOHOL; SILICON DIOXIDE; STYRENE/ACRYLAMIDE COPOLYMER (MW 500000); ETHYLHEXYLGLYCERIN; ALKYL (C12-15) BENZOATE; ALUMINA; CAMELLIA SINENSIS LEAF; CUCUMBER; CETYL PEG/PPG-10/1 DIMETHICONE (HLB 2); PUNICA GRANATUM FRUIT JUICE; SORBITAN OLIVATE; ALOE VERA LEAF; VITIS VINIFERA (GRAPE) SEED; DIMETHICONE 200

ACTIVE INGREDIENT

Titanium Dioxide 6%, Zinc Oxide 5%

PURPOSE

Sunscreen

INDICATIONS AND USAGE

Helps prevent sunscreen. If used as directed with other sun protection measures (see Directions), decreases the risk of skin cancer and early skin aging caused by the sun.

WARNINGS

For external use only.

Do not use on damaged or broken skin.

When using this product avoid contact with eyes. Rinse with water to remove.

Stop use and ask a doctor if rash or irritation develops and lasts.

KEEP OUT OF REACH OF CHILDREN

If product is swallowed, get medical help or contact a poison Control Center right away.

DOSAGE AND ADMINISTRATION

For sunscreen use: shake well before use, apply liberally 15 minutes before sun exposure and as needed, reapply: after 40 minutes of swimming or sweating, immediately after towel drying, and at least every 2 hours.

Sun Protection Measures. Spending time in the sun increases your risk of skin cancer and early skin aging. To decrease this risk, regularly use a sunscreen with a Broad Spectrum SPF value of 15 or higher and other sun protection measures including: limit time in the sun, especially from 10 am - 2 pm, wear long-sleeved shirts, pants, hats, and sunglasses.

Children under 6 months of age: ask a doctor.

INACTIVE INGREDIENT

Aloe barbadensis leaf extract, alumina, aluminum starch octenylsuccinate, benzyl alcohol, C12-15 alkyl benzoate, camellia sinensis leaf extract, cetyl PEG/PPG-10/1 dimethicone, cucumis sativus (cucumber) fruit extract, dimethicone, disodium EDTA, ethyhexyl palmitate, ethyhexylglycerin, glycerin, hydrogen dimethicone, propanediol, punica granatum fruit juice, silica, sodium chloride, sorbitan olivate, styrene/acrylates copolymer, vitis vinifera (grape) seed extract, water.